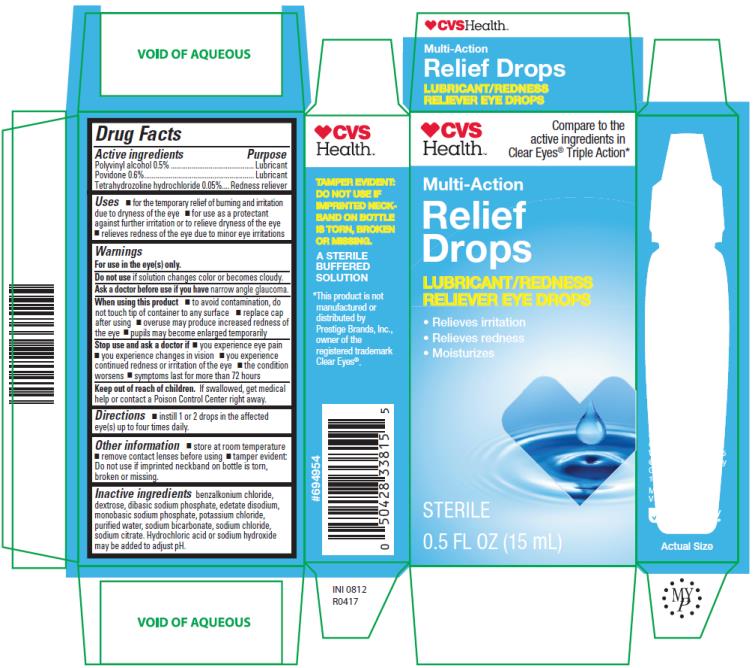 DRUG LABEL: Multi-Action Relief
NDC: 59390-156 | Form: SOLUTION/ DROPS
Manufacturer: Altaire Pharmaceuticals Inc.
Category: otc | Type: HUMAN OTC DRUG LABEL
Date: 20231209

ACTIVE INGREDIENTS: POLYVINYL ALCOHOL, UNSPECIFIED 5 mg/1 mL; POVIDONE 6 mg/1 mL; TETRAHYDROZOLINE HYDROCHLORIDE 0.5 mg/1 mL
INACTIVE INGREDIENTS: BENZALKONIUM CHLORIDE; DEXTROSE; SODIUM PHOSPHATE, DIBASIC; EDETATE DISODIUM; SODIUM PHOSPHATE, MONOBASIC; POTASSIUM CHLORIDE; WATER; SODIUM BICARBONATE; SODIUM CHLORIDE; SODIUM CITRATE

Multi-Action Relief Drops

Multi-Action Relief Drops 15mLNDC 59390-156-13

Drug Facts

Active ingredients

Polyvinyl alcohol 0.5%

Povidone 0.6%

Tetrahydrozoline hydrochloride 0.05%

Purpose

Lubricant

Lubricant

Redness Reliever

Uses

- for the temporary relief of burning and irritation due to dryness of the eye
- for use as a protectant against further irritation or to relieve dryness of the eye
- relieves redness of the eye due to minor eye irritations

Warnings

Forusein the eye(s) only.

Do not useif

solution changes color or becomes cloudy.

Ask a doctor before use if you have

narrow angle glaucoma.

When using this product

- to avoid contamination, do not touch tip ofcontainer to any surface
- replace cap after using
- overuse may produce increased redness of the eye
- pupils may become enlarged temporarily

Stop use and ask a doctor if

- you experience eye pain
- you experience changes in vision
- you experience continued redness or irritation of the eye
- the condition worsens
- symptoms last for more than 72 hours

Keepoutofreach of children.

If swallowed, get medical helporcontact a Poison Control Center right away.

Directions

- Instill 1 or 2 drops in the affected eye(s) up to four times daily.

Other Information

- store at room temperature.
- remove contact lenses before using
- tamper evident: Do not use if imprinted neckband on bottle is torn, broken or missing.

Inactive ingredients

benzalkonium chloride, dextrose, dibasic sodium phosphate, edetate disodium, monobasic sodium phosphate, potassium chloride, purified water, sodium bicarbonate, sodium chloride, sodium citrate. Hydrochloric acid or sodium hydroxide may be added to adjust pH.

PRINCIPAL DISPLAY PANEL

Multi-Action RELIEF DROPSLUBRICANT/REDNESSRELIEVER EYE DROPSSTERILE0.5 FL OZ (15mL)